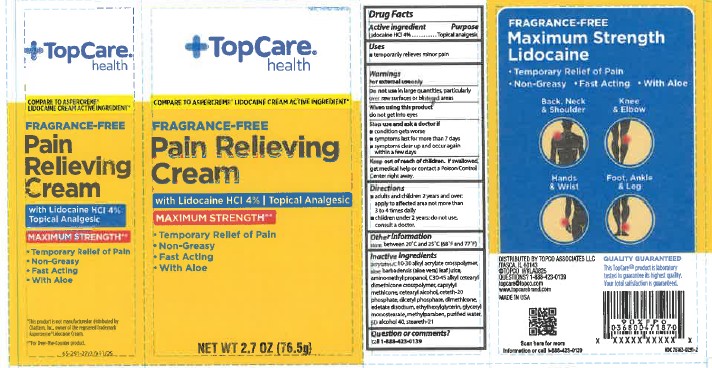 DRUG LABEL: TopCare Pain Relieving Cream
NDC: 76162-291 | Form: CREAM
Manufacturer: Topco Associates, LLC
Category: otc | Type: HUMAN OTC DRUG LABEL
Date: 20260116

ACTIVE INGREDIENTS: LIDOCAINE HYDROCHLORIDE 40 mg/1 g
INACTIVE INGREDIENTS: METHYLPARABEN; AMINOMETHYL PROPANOL; EDETATE DISODIUM; C30-45 ALKYL CETEARYL DIMETHICONE CROSSPOLYMER; DICETYL PHOSPHATE; ETHYLHEXYLGLYCERIN; STEARETH-21; ALCOHOL; ALOE BARBADENSIS LEAF JUICE; WATER; CETEARYL ALCOHOL; DIMETHICONE; GLYCERYL MONOSTEARATE; CAPRYLYL METHICONE; ACRYLATES/C10-30 ALKYL ACRYLATE CROSSPOLYMER (60000 MPA.S); CETETH-20 PHOSPHATE

TopCare Lidocaine Cream

ACTIVE INGREDIENT

Lidocaine HCl 4%

INDICATIONS AND USAGE

temporarily relieves minor pain

PURPOSE

Topical analgesic

WARNINGS

For external use only

DO NOT USE

In large quantities, particularly over raw surfaces or blistered areas

Stop use

- condition gets worse
- symptoms last for more than 7 days
- symptoms clear up and occur again within a few days

WHEN USING

do not get into eyes

STOP USE

- condition gets worse
- symptoms last for more than 7 days
- symptoms clear up and occur again within a few days

KEEP OUT OF REACH OF CHILDREN

If swallowed, get medical help or contact a Poison Control Center right away.

Directions

- adults and children 2 years and over: apply to affected area not more than 3 to 4 times daily
- children under 2 years: do not use, consult a doctor.

Other information

store at controlled room temperature 20°-25°C (68°-77°F)

INACTIVE INGREDIENT

acrylates/C10-30 alkyl acrylate crosspolymer, aloe barbadensis (aloe vera) leaf juice, aminomethyl propanol,
C30-45 alkyl cetearyl dimethicone crosspolymer, caprylyl methicone, cetearyl alcohol, ceteth-20 phosphate, dicetyl phosphate, dimethicone, edetate disodium, ethylhexylglycerin, glyceryl monostearate, methylparaben, purified water, SD alcohol 40, steareth-21

uses:

added temporarily relieves pain.

Directions

Added the required directions

PACKAGE LABEL

TopCare Health

Fragrance-free

Pain Relieving Cream

with Lidocaine HCl 4% Topical Analgesic

Maximum Strength

Temporary Relief of Pain

Non-Greasy

Fast Acting

with Aloe

Net Wt 2.7oz (76.5g)